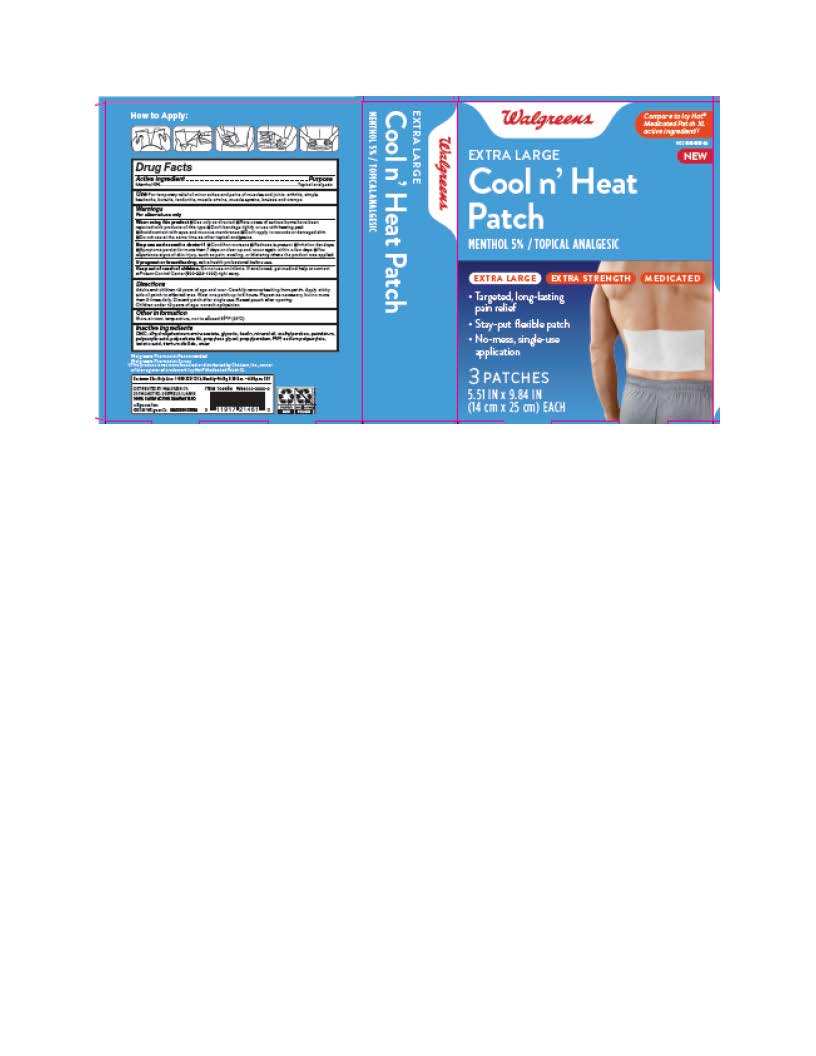 DRUG LABEL: Extra Large Cool and Heat Patch
NDC: 0363-9905 | Form: PATCH
Manufacturer: Walgreen Company
Category: otc | Type: HUMAN OTC DRUG LABEL
Date: 20241218

ACTIVE INGREDIENTS: MENTHOL 5 g/100 g
INACTIVE INGREDIENTS: PETROLATUM; MINERAL OIL; DIHYDROXYALUMINUM AMINOACETATE; GLYCERIN; KAOLIN; METHYLPARABEN; SODIUM POLYACRYLATE (2500000 MW); POLYACRYLIC ACID (250000 MW); POLYSORBATE 80; PROPYLENE GLYCOL; PROPYLPARABEN; POVIDONE, UNSPECIFIED; CARBOXYMETHYLCELLULOSE; TARTARIC ACID; TITANIUM DIOXIDE; WATER

Extra Large Cool and Heat Patch

ACTIVE INGREDIENT

Active Ingredient ...............................................................................................Purpose
Menthol 5%...............................................................................................Topical Analgesic

INACTIVE INGREDIENT

CMC, Dihydroxy aluminum Aminoacetate, Glycerin, Kaolin, Mineral Oil, Methylparaben, Petrolatum, Polyacrylic Acid, Polysorbate 80, Propylene Glycol, Propylparaben, PVP, Sodium Polyacrylate, Tartaric Acid, Titanium Dioxide, Water

KEEP OUT OF REACH OF CHILDREN

Do not use on infants. If swallowed, get medical help or contact a Poison Control Center (800-222-1222) right away.

INDICATIONS & USAGE

For temporary relief of minor aches and pains of muscles and joints: arthritis, simple backache, bursitis, tendonitis, muscle strains, muscle sprains, bruises and cramps.

WARNINGS

For External Use Only.

DOSAGE & ADMINISTRATION

Adults and children over 12 years: Carefully remove backing from patch. Apply sticky side of patch to affected area.

Wear one patch up to 8 hours. Repeat as necessary, but no more than 3 times daily. Reseal pouch after opening.

Children 12 years or younger: Consult a physician.

PURPOSE

Topical Analgesic

When using this product ■ Use only as directed ■ Rare cases of serious burns have been reported with products of this type ■ Don’t bandage tightly or use with heating pad ■ Avoid contact with eyes and mucous membranes ■ Don’t apply to wounds or damaged skin ■ Do not use at the same time as other topical analgesics.

Stop use and ask a doctor

■ Condition worsens ■ Redness is present ■ Irritation develops ■ Symptoms persist for more than 7 days or clear up and occur again within a few days ■ You experience signs of skin injury, such as pain, swelling, or blistering where the product was applied.

If pregnant or breastfeeding

ask a health professional before use.